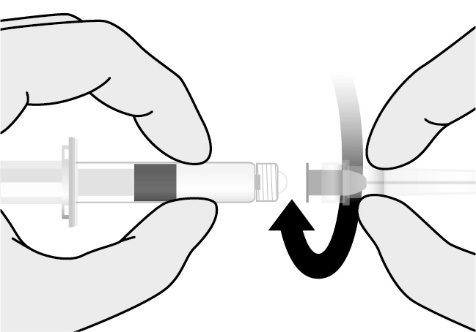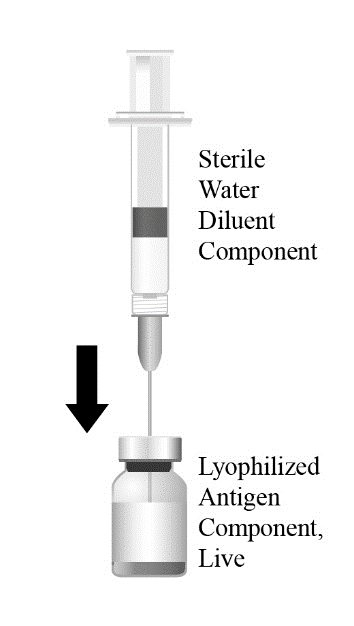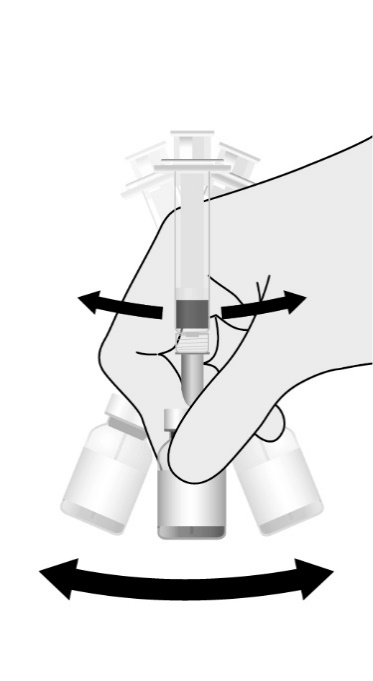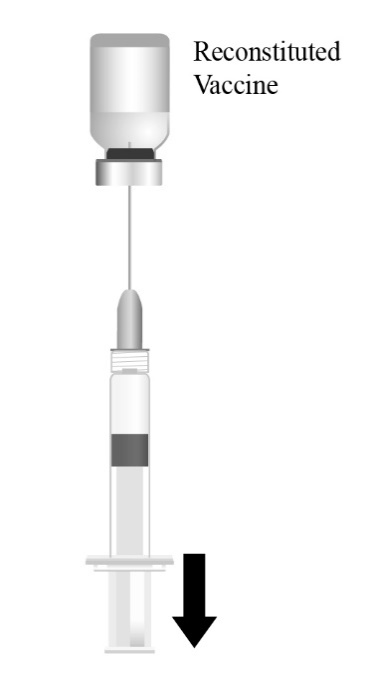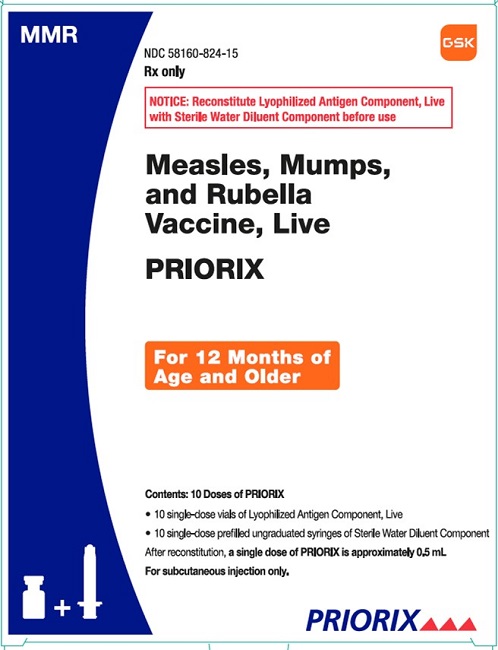 DRUG LABEL: Priorix
NDC: 58160-824 | Form: KIT | Route: SUBCUTANEOUS
Manufacturer: GlaxoSmithKline Biologicals SA
Category: other | Type: VACCINE LABEL
Date: 20251114

ACTIVE INGREDIENTS: MEASLES VIRUS STRAIN SCHWARTZ ATTENUATED CHICK EMBRYO FIBROBLASTS LIVE ANTIGEN 2512 [CCID_50]/0.5 mL; MUMPS VIRUS STRAIN RIT-4385 ATTENUATED CHICK EMBRYO FIBROBLASTS LIVE ANTIGEN 15842 [CCID_50]/0.5 mL; RUBELLA VIRUS STRAIN WISTAR RA 27/3 LIVE ANTIGEN 1995 [CCID_50]/0.5 mL
INACTIVE INGREDIENTS: ANHYDROUS LACTOSE; SORBITOL; MANNITOL; AMINO ACIDS, SOURCE UNSPECIFIED; WATER

HIGHLIGHTS OF PRESCRIBING INFORMATION

These highlights do not include all the information needed to use PRIORIX safely and effectively. See full prescribing information for PRIORIX.
PRIORIX (Measles, Mumps, and Rubella Vaccine, Live) for injectable suspension, for subcutaneous use
Initial U.S. Approval: 2022

RECENT MAJOR CHANGES

Contraindications, Immunosuppression (4.2) | 11/2025

1 INDICATIONS AND USAGE

PRIORIX is a vaccine indicated for active immunization for the prevention of measles, mumps, and rubella in individuals 12 months of age and older. (1)

2 DOSAGE AND ADMINISTRATION

For subcutaneous use.

Each dose is approximately 0.5 mL.

- The first dose is administered at 12 through 15 months of age. (2.1)
- The second dose is administered at 4 through 6 years of age. (2.1)

3 DOSAGE FORMS AND STRENGTHS

For injectable suspension. PRIORIX is supplied as a single-dose vial of Lyophilized Antigen Component, Live to be reconstituted with the accompanying prefilled syringe of Sterile Water Diluent Component. A single dose after reconstitution is approximately 0.5 mL. (3)

4 CONTRAINDICATIONS

- Severe allergic reaction (e.g., anaphylaxis) to any component of PRIORIX, or after a previous dose of any measles, mumps, and rubella virus-containing vaccine. (4.1)
- Severe immunodeficiency. (4.2)
- Pregnancy. (4.3, 8.1)

5 WARNINGS AND PRECAUTIONS

- There is a risk of febrile seizure following administration of PRIORIX. (5.2)
- Thrombocytopenia and thrombocytopenic purpura have been reported following vaccination with PRIORIX. (5.3)
- Syncope (fainting) can occur in association with administration of injectable vaccines, including PRIORIX. Procedures should be in place to avoid injury from fainting. (5.4)
- The tip caps of the prefilled syringes contain natural rubber latex, which may cause allergic reactions. (5.5)

6 ADVERSE REACTIONS

Most common solicited adverse reactions in clinical trials participants:

- 12 through 15 months of age: local reactions were pain (26%) and redness (25%); systemic reactions were irritability (63%), loss of appetite (45%), drowsiness (45%), and fever (35%). (6.1)
- 4 through 6 years of age: local reactions were pain (41%), redness (22%), and swelling (11%); systemic reactions were loss of appetite (21%), drowsiness (27%), and fever (24%). (6.1)
- 7 years of age and older: local reactions were pain (12%) and redness (12%). (6.1)

To report SUSPECTED ADVERSE REACTIONS, contact GlaxoSmithKline at 1-888-825-5249 or VAERS at 1-800-822-7967 or www.vaers.hhs.gov.

7 DRUG INTERACTIONS

- Administration of immune globulins and other blood products concurrently with PRIORIX may interfere with the expected immune response to the vaccine. (7.2)
- PRIORIX may result in a temporary suppression of tuberculin reactivity. (7.3)

8 USE IN SPECIFIC POPULATIONS

- Do not use during pregnancy. (8.1)
- Avoid pregnancy for 1 month following vaccination with PRIORIX. (8.1)

FULL PRESCRIBING INFORMATION

1 INDICATIONS AND USAGE

PRIORIX is a vaccine indicated for active immunization for the prevention of measles, mumps, and rubella in individuals 12 months of age and older.

2 DOSAGE AND ADMINISTRATION

For subcutaneous use.

2.1 Dose and Schedule

After reconstitution, a single dose of PRIORIX is approximately 0.5 mL.

Administer according to the following schedule:

- First dose – 12 through 15 months of age
- Second dose – 4 through 6 years of age

If PRIORIX is not administered according to this schedule and 2 doses of measles-, mumps- and rubella-virus vaccine are recommended for an individual, there should be a minimum of 4 weeks between the first and second dose.

PRIORIX may be administered as a second dose to individuals who have received a first dose of another measles, mumps and rubella virus-containing vaccine.

2.2 Preparation

Reconstitute the Lyophilized Antigen Component, Live only with the accompanying Sterile Water Diluent Component to form PRIORIX. The reconstituted vaccine should be a clear peach- to fuchsia pink-colored suspension. Parenteral drug products should be inspected visually for particulate matter and discoloration prior to administration, whenever solution and container permit. If either of these conditions exists, do not administer the vaccine.

Figure 1. Hold the prefilled syringe of Sterile Water Diluent Component by the barrel and unscrew the syringe cap by twisting it counterclockwise. Align the needle to the axis of the syringe and attach by gently connecting the needle hub into the Luer Lock Adaptor (LLA) and rotate a quarter turn clockwise until you feel it lock.

Figure 2. Cleanse the Lyophilized Antigen Component, Live vial stopper. Transfer the entire contents of the prefilled syringe into the vial.

Figure 3. Shake the vial well until the powder is completely dissolved. Do not invert the vial while shaking.

Figure 4. After reconstitution, withdraw the entire contents of the reconstituted vaccine into the same syringe and after changing the needle, administer subcutaneously.

2.3 Administration

Administer PRIORIX immediately after reconstitution. If not used immediately, store refrigerated between 36° and 46°F (2° and 8°C) and administer within 8 hours. Discard reconstituted vaccine if not used within 8 hours.

3 DOSAGE FORMS AND STRENGTHS

For injectable suspension. PRIORIX is supplied as a single-dose vial of Lyophilized Antigen Component, Live to be reconstituted with the accompanying prefilled syringe of Sterile Water Diluent Component. A single dose after reconstitution is approximately 0.5 mL.

4 CONTRAINDICATIONS

4.1 Severe Allergic Reactions

Do not administer PRIORIX to individuals with a history of severe allergic reactions (e.g., anaphylaxis) to any component of the vaccine or after a previous dose of any measles, mumps, and rubella virus-containing vaccine [see Description (11)].

4.2 Immunosuppression

Do not administer PRIORIX to individuals who are immunodeficient or immunosuppressed due to disease or medical therapy. These individuals are at risk of disseminated vaccine virus infection [see Drug Interactions (7.1)].

4.3 Pregnancy

Do not administer PRIORIX to individuals who are pregnant. Pregnancy should be avoided for 1 month after vaccination [see Use in Specific Populations (8.1)].

5 WARNINGS AND PRECAUTIONS

5.1 Allergic Vaccine Reactions

Appropriate medical treatment used to manage immediate allergic reactions must be available in the event an acute anaphylactic reaction occurs following administration of PRIORIX.

5.2 Febrile Seizures

There is a risk of febrile seizure following immunization with PRIORIX [see Adverse Reactions (6.1)].

5.3 Thrombocytopenia

Thrombocytopenia and thrombocytopenic purpura have been reported following vaccination with PRIORIX [see Adverse Reactions (6.2)].

5.4 Syncope

Syncope (fainting) can occur in association with administration of injectable vaccines, including PRIORIX. Procedures should be in place to avoid injury from fainting.

5.5 Latex

The tip caps of the prefilled syringes of diluent contain natural rubber latex, which may cause allergic reactions.

5.6 Risk of Vaccine Virus Transmission

Live attenuated rubella vaccine virus has been detected in the nose and throat of individuals 7 to 28 days after vaccination with a rubella virus containing vaccine, but no documented confirmed cases of transmitted rubella vaccine virus have been reported.^1

5.7 Limitation of Vaccine Effectiveness

Vaccination with PRIORIX may not protect all susceptible individuals.

6 ADVERSE REACTIONS

The most commonly reported (≥10%) solicited adverse reactions in the following age groups in clinical trials were:

- Age 12 through 15 months – local: pain (26%) and redness (25%); systemic: irritability (63%), loss of appetite (45%), drowsiness (45%), and fever (35%)
- Age 4 through 6 years – local: pain (41%), redness (22%), and swelling (11%); systemic: loss of appetite (21%), drowsiness (27%), and fever (24%)
- Age 7 years and older – local: pain (12%) and redness (12%)

6.1 Clinical Trials Experience

Because clinical trials are conducted under widely varying conditions, adverse reaction rates observed in the clinical trials of a vaccine cannot be directly compared with rates in the clinical trials of another vaccine and may not reflect the rates observed in practice.

The safety of PRIORIX was evaluated in 6 clinical studies, in which a total of 12,151 participants (6,391 in the United States) received at least 1 dose of PRIORIX: 8,780 children (4,148 in the United States) 12 through 15 months of age; 2,917 children (1,950 in the United States) 4 through 6 years of age; and 454 adults and children (293 in the United States) 7 years of age and older. Across the 6 studies, participants who received PRIORIX are as follows: 51.6% were male; 64.6% were White, 18.4% were Asian, 6.1% were Black, and 10.9% were of other racial groups (including American Indian/Native American, Native Hawaiian/Pacific Islander, Arabic/North African and Other); and 14.3% were of Hispanic/Latino ethnicity. The racial/ethnic distribution of participants who received PRIORIX and M‑M‑R II was similar.

Children 12 through 15 Months of Age Who Received PRIORIX as a First Dose

In a randomized, observer-blind, controlled clinical study (Study 1, NCT01702428) conducted in 5 countries (United States [including Puerto Rico], Estonia, Finland, Mexico and Spain), 5,003 participants 12 through 15 months of age received a first dose of PRIORIX (n = 3,714) or M‑M‑R II (n = 1,289) given concomitantly with HAVRIX (Hepatitis A Vaccine) and VARIVAX (Varicella Virus Vaccine Live, Merck & Co., Inc.); children enrolled in the United States also received PREVNAR 13 (Pneumococcal 13-valent Conjugate Vaccine, Pfizer Inc.) concomitantly. In the overall population, 51.3% were male; 75.6% were White, 4.8% were Black, 3.5% were Asian, 16.1% were of other racial groups (including American Indian/Native American, Native Hawaiian/Pacific Islander, Arabic/North African and Other); and 18.6% were of Hispanic/Latino ethnicity. The median age of participants was 12 months (range: 11 to 16 months). Local solicited adverse reactions were recorded by parents or guardians using standardized diary cards for 4 days. Systemic solicited adverse reactions of drowsiness, loss of appetite, and irritability were collected for 15 days, and fever, rash, parotid/salivary gland swelling, febrile convulsions, and signs of meningeal irritation (i.e., neck stiffness with or without photophobia or headache) were collected for 43 days (Table 1). Unsolicited adverse events that occurred within 43 days following vaccination were recorded using diary cards supplemented by medical review. Data on solicited adverse reactions and unsolicited adverse events were transcribed into the study database during an on-site visit on Day 42 and via telephone contact on Day 180.

Table 1. Incidence of Solicited Local and Systemic Adverse Reactions after the First Dose of PRIORIX Compared with M-M-R II in Children 12 through 15 Months of Age (Study 1, NCT01702428, Total Vaccinated Cohort)a
Adverse Reaction | PRIORIX; n (%) | M-M-R II; n (%)
Local (within 4 Daysb) | N = 3,555 | N = 1,242
Pain | 919 (25.9%) | 349 (28.1%)
Redness | 870 (24.5%) | 313 (25.2%)
Swelling | 318 (8.9%) | 133 (10.7%)
Systemic (within 15 Daysb) | N = 3,566 | N = 1,243
Drowsiness | 1601 (44.9%) | 586 (47.1%)
Irritability | 2258 (63.3%) | 819 (65.9%)
Loss of appetite | 1608 (45.1%) | 548 (44.1%)
Systemic (within 43 Daysb) | N = 3,566 | N = 1,243
Measles/rubella-like rash | 235 (6.6%) | 77 (6.2%)
Fever (defined as temperature ≥38°C/100.4°F) | 1244 (34.9%) | 412 (33.1%)
Parotid/salivary gland swelling | 0 | 0
Febrile convulsions | 7 (0.2%) | 3 (0.2%)
Signs of meningeal irritationc | 3 (0.1%) | 0
Total vaccinated cohort for safety included all vaccinated participants for whom safety data were available.
N = Number of participants.
n = Number of participants presenting with solicited adverse reaction described.
a HAVRIX and VARIVAX were administered concomitantly with PRIORIX or M-M-R II; participants in the U.S. also received PREVNAR 13 concomitantly with PRIORIX (n = 1,847) or M-M-R II (n = 654).
b 4 Days, 15 Days, and 43 Days included the day of vaccination and the subsequent 3, 14, and 42 days, respectively.
c Neck stiffness with or without photophobia or headache.

Children 12 through 15 Months of Age Who Received a Second Dose of PRIORIX 6 Weeks after the First Dose

In a randomized, observer-blind, controlled clinical study (Study 2, NCT01681992) conducted in six countries (United States [including Puerto Rico], Czech Republic, Finland, Malaysia, Spain and Thailand), 4,516 participants 12 through 15 months of age received a first dose of PRIORIX (n = 2,990) or M‑M‑R II (n = 1,526) followed by a second dose of the same vaccine 6 weeks later. The first dose was given concomitantly with HAVRIX and VARIVAX; children enrolled in the United States (including Puerto Rico) also received PREVNAR 13 concomitantly. In the overall population, 51.7% were male; 68.4% were White, 24.4% were Asian, 3.2% were Black, and 4.0% were of other racial groups (including American Indian/Native American, Native Hawaiian/Pacific Islander, Arabic/North African and Other); and 5.6% were of Hispanic/Latino ethnicity. The median age of participants was 12 months (range: 11 to 16 months). Local solicited adverse reactions were recorded by parents or guardians using standardized diary cards for 4 days, and systemic adverse reactions of fever, rash, parotid/salivary gland swelling, febrile convulsions, and signs of meningeal irritation (i.e., neck stiffness with or without photophobia or headache) were collected for 43 days. Unsolicited adverse events that occurred within 43 days following vaccination were recorded using diary cards supplemented by medical review. Data on solicited adverse reactions and unsolicited adverse events were transcribed into the study database during on-site visits on Day 42, Day 84, and Day 222. The safety profile of PRIORIX following the second dose was similar to the safety profile following the first dose of PRIORIX.

Children 4 through 6 Years of Age Who Received PRIORIX as a Second Dose of Measles, Mumps, and Rubella Vaccine

In a randomized, observer-blind, controlled clinical study (Study 3, NCT01621802) conducted in 3 countries (United States, South Korea, and Taiwan), 4,007 participants 4 through 6 years of age received PRIORIX (n = 2,917) or M-M-R II (n = 1,090) as a second dose following administration of an initial dose of a combined measles, mumps, and rubella virus-containing vaccine in the second year of life. PRIORIX and M-M-R II were given concomitantly with KINRIX (DTaP-IPV) [Diphtheria and Tetanus Toxoids and Acellular Pertussis Adsorbed and Inactivated Poliovirus Vaccine] and VARIVAX in a subset of subjects (n = 802 receiving PRIORIX, n = 298 receiving M-M-R II) enrolled in the United States. In the overall population, 52.5% were male; 42.4% were White, 37.2% were Asian, 8.2% were Black, and 12.3% were of other racial groups (including American Indian/Native American, Native Hawaiian/Pacific Islander, Arabic/North African and Other) and 17.2% were of Hispanic/Latino ethnicity. The median age of participants was 4 years (range: 3 to 6 years). In a subset of participants who received concomitantly administered vaccines, data on local solicited adverse reactions were recorded by parents or guardians using standardized diary cards for 4 days. Systemic solicited adverse reactions of drowsiness and loss of appetite were collected for 4 days, and fever, rash, parotid/salivary gland swelling, febrile convulsions, and signs of meningeal irritation (i.e., neck stiffness with or without photophobia or headache) were collected for 43 days (Table 2). Unsolicited adverse events that occurred within 43 days following vaccination were recorded using diary cards supplemented by medical review. Data on solicited adverse reactions and unsolicited adverse events were transcribed into the study database during an on‑site visit on Day 42 and via telephone contact on Day 180.

Table 2. Incidence of Solicited Local and Systemic Adverse Reactions after the Second Dose of PRIORIX Compared with M-M-R II Concomitantly Administered with KINRIX and VARIVAX in Children 4 through 6 Years of Age (Study 3, NCT01621802, Total Vaccinated Cohort)
Adverse Reaction | PRIORIX; n (%) | M-M-R II; n (%)
Local (within 4 Daysa) | N = 727 | N = 267
Pain | 295 (40.6%) | 109 (40.8%)
Redness | 157 (21.6%) | 69 (25.8%)
Swelling | 82 (11.3%) | 28 (10.5%)
Systemic (within 4 Daysa) | N = 731 | N = 268
Drowsiness | 199 (27.2%) | 72 (26.9%)
Loss of appetite | 154 (21.1%) | 59 (22.0%)
Systemic (within 43 Daysa) | N = 731 | N = 268
Measles/rubella-like rash | 14 (1.9%) | 5 (1.9%)
Fever (defined as temperature ≥38°C/100.4°F) | 177 (24.2%) | 67 (25.0%)
Parotid/salivary gland swelling | 0 | 0
Febrile convulsions | 0 | 0
Signs of meningeal irritationb | 0 | 2 (0.7%)
Total vaccinated cohort for safety included all vaccinated participants for whom safety data were available.
N = Number of participants.
n = Number of participants presenting with solicited adverse reaction described.
a 4 Days and 43 Days included the day of vaccination and the subsequent 3 and 42 days, respectively.
b Neck stiffness with or without photophobia or headache.

Individuals 7 Years of Age and Older Who Received PRIORIX as a Second Dose of Measles, Mumps, and Rubella Vaccine

In a randomized, observer-blind, controlled clinical study (Study 4, NCT02058563) conducted in 3 countries (United States, Slovakia, and Estonia), 860 participants 7 years of age and older received PRIORIX (n = 426) or M-M-R II (n = 434) as a second dose following previous administration of a combined measles, mumps, and rubella virus-containing vaccine. Participants 7 through 17 years were enrolled if they had received one dose of a combined measles, mumps, and rubella virus-containing vaccine on or after their first birthday and participants 18 years of age or older were enrolled if they previously received at least one dose of a combined measles, mumps, and rubella virus-containing vaccine. In the overall population, 46.2% were male; 73.8% were White, 0.2% were Asian, 24.0% were Black, and 1.9% were of other racial groups (including American Indian/Native American, Native Hawaiian/Pacific Islander, Arabic/North African and Other) and 13.3% were of Hispanic/Latino ethnicity. The median age of participants was 26 years (range: 7 to 59 years). Data on solicited local and systemic adverse reactions were recorded by the participants or their parents or guardians using standardized diary cards for 4 days and 43 days, respectively (Table 3). Unsolicited adverse events that occurred within 43 days following vaccination were recorded using diary cards supplemented by medical review. Data on solicited adverse reactions and unsolicited adverse events were transcribed into the study database during an on-site visit on Day 42 and via telephone contact on Day 180.

Table 3. Incidence of Solicited Local and Systemic Adverse Reactions after PRIORIX as a Second Dose Compared with M-M-R II in Individuals 7 Years of Age and Older (Study 4, NCT02058563, Total Vaccinated Cohort)a
 | PRIORIX; n (%) | M-M-R II; n (%)
Local (within 4 Daysb) | N = 405 | N = 422
Pain | 49 (12.1%) | 47 (11.1%)
Redness | 48 (11.9%) | 50 (11.8%)
Swelling | 23 (5.7%) | 29 (6.9%)
Systemic (within 43 Daysb) | N = 405 | N = 422
Fever (defined as temperature ≥38°C/100.4°F) | 11 (2.7%) | 23 (5.5%)
Measles/rubella-like rash | 0 | 2 (0.5%)
Joint pain (arthralgia/arthritis) | 8 (2.0%) | 4 (0.9%)
Parotid/salivary gland swelling | 1 (0.2%) | 0
Signs of meningeal irritationc | 1 (0.2%) | 1 (0.2%)
Total vaccinated cohort for safety included all vaccinated participants for whom safety data were available.
N = Number of participants.
n = Number of participants presenting with solicited adverse reaction described.
a Participants received a first dose of either M-M-R II, PRIORIX, or a non-U.S. combined measles, mumps, rubella and varicella virus vaccine.
b 4 Days and 43 Days included the day of vaccination and the subsequent 3 and 42 days, respectively.
c Neck stiffness with or without photophobia or headache.

6.2 Postmarketing Experience

In addition to adverse reactions reported from clinical trials, the following adverse reactions have been identified during postmarketing use of PRIORIX. Because these reactions are reported voluntarily from a population of uncertain size, it is not always possible to reliably estimate their frequency or establish a causal relationship to vaccination with PRIORIX.

Blood and Lymphatic System Disorders

Thrombocytopenia, thrombocytopenic purpura.

Vascular Disorders

Vasculitis (including Henoch-Schönlein purpura and Kawasaki syndrome).

Immune System Disorders

Anaphylactic reactions.

Infections and Infestations

Meningitis, measles-like illness, mumps-like illness (including orchitis, epididymitis, and parotitis).

Musculoskeletal and Connective Tissue Disorders

Arthralgia, arthritis.

Nervous System Disorders

Encephalitis, cerebellitis, cerebellitis-like symptoms (including transient gait disturbance and transient ataxia), Guillain-Barré syndrome, transverse myelitis, peripheral neuritis, afebrile seizures, syncope.

Skin and Subcutaneous Tissue Disorders

Erythema multiforme, chronic cutaneous granulomas with rubella vaccine virus detected by biopsy.

7 DRUG INTERACTIONS

7.1 Immunosuppressive Drugs

Do not administer PRIORIX to individuals who are immunosuppressed due to medical therapy. Vaccination with PRIORIX can result in disseminated disease due to vaccine viruses in individuals on immunosuppressive drugs [see Contraindications (4.2)].

7.2 Immune Globulins and Blood Products

Immune globulins and other blood products administered concomitantly with PRIORIX contain antibodies that may interfere with vaccine virus replication and decrease the expected immune response. The U.S. Centers for Disease Control and Prevention (CDC) has specific recommendations for intervals between administration of antibody containing products and live virus vaccines.

7.3 Tuberculin Skin Testing

PRIORIX may result in a temporary suppression of tuberculin reactivity. Therefore, if a tuberculin test is to be done, it should be administered either any time before, simultaneously with, or at least 4 weeks after PRIORIX to avoid false-negative results.

7.4 Use with Other Live Viral Vaccines

PRIORIX can be administered concomitantly with other live viral vaccines. If not given concomitantly, PRIORIX should be given 1 month before or 1 month after administration of other live viral vaccines to avoid potential for immune interference.

8 USE IN SPECIFIC POPULATIONS

8.1 Pregnancy

Risk Summary

PRIORIX contains live attenuated measles, mumps, and rubella viruses. The vaccine is contraindicated for use in pregnant women because infection during pregnancy with the wild-type viruses is associated with maternal and fetal adverse outcomes. Pregnancy should be avoided for 1 month after vaccination [see Contraindications (4.3), Patient Counseling Information (17)].

Reports have indicated that contracting wild-type measles during pregnancy enhances fetal risk, including increased rates of spontaneous abortion, stillbirth, premature delivery and congenital defects.^2,3 Wild-type mumps virus infection during the first trimester of pregnancy may increase the rate of spontaneous abortion. Pregnant women infected with wild-type rubella virus are at increased risk for miscarriage or stillbirth, and their infants are at risk for congenital rubella syndrome (CRS).^1

Postmarketing surveillance has identified a case of CRS following inadvertent vaccination of a pregnant woman with a measles, mumps, and rubella virus containing vaccine from an unknown manufacturer^4 [see Data].

There are no animal studies with PRIORIX to inform use during pregnancy.

All pregnancies have a risk of birth defect, loss, or other adverse outcomes. In the U.S. general population, the estimated background risk of major birth defects and miscarriage in clinically recognized pregnancies is 2% to 4% and 15% to 20%, respectively.

Data

Human Data: Postmarketing surveillance has identified a case of CRS associated with a rubella virus strain belonging to the genotype that includes the rubella virus strain Wistar RA 27/3 contained in PRIORIX. The infant with CRS was born to a pregnant woman who was inadvertently vaccinated at 5 weeks gestation with a measles, mumps, and rubella virus containing vaccine from an unknown manufacturer.^4

8.2 Lactation

Risk Summary

It is not known whether the vaccine components of PRIORIX are excreted in human milk. Data are not available to assess the effects of PRIORIX on the breastfed infant or on milk production/excretion. Studies have shown that lactating postpartum women vaccinated with live attenuated rubella vaccine may secrete the virus in breast milk and transmit it to breast‑fed infants.^5,6 In the breast-fed infants with serological evidence of rubella virus vaccine strain antibodies, none exhibited severe disease; however, one exhibited mild clinical illness typical of acquired rubella.^7,8

The developmental and health benefits of breastfeeding should be considered along with the mother’s clinical need for PRIORIX and any potential adverse effects on the breastfed child from PRIORIX or from the underlying maternal condition. For preventive vaccines, the underlying maternal condition is susceptibility to disease prevented by the vaccine.

8.4 Pediatric Use

Safety and effectiveness of PRIORIX in infants younger than 12 months have not been established.

8.5 Geriatric Use

Clinical studies of PRIORIX did not include participants 65 years of age and older to determine whether they respond differently from younger participants.

11 DESCRIPTION

PRIORIX (Measles, Mumps, and Rubella Vaccine, Live) is an injectable suspension for subcutaneous use. PRIORIX is supplied as a sterile, Lyophilized Antigen Component, Live which is reconstituted at the time of use with the accompanying Sterile Water Diluent Component. The Lyophilized Antigen Component, Live is a whitish to slightly pink powder, a portion of which may be yellowish to slightly orange.

PRIORIX contains the Schwarz strain of live attenuated measles virus, the RIT 4385 strain of live attenuated mumps virus (derived from the Jeryl Lynn strain), both propagated in chick‑embryo fibroblasts from embryonated eggs of specific pathogen-free flocks and the Wistar RA 27/3 strain of live attenuated rubella virus propagated in MRC-5 human diploid cells. The 3 virus strains are cultured in media containing amino acids, a small amount of neomycin sulfate and bovine serum albumin and are stabilized after multiple washing steps in media free from antibiotics and albumin. The attenuated measles, mumps and rubella viruses are then mixed with a stabilizer prior to lyophilization.

After reconstitution, each approximately 0.5-mL dose contains not less than 3.4 log10 Cell Culture Infective Dose 50% (CCID50) of measles virus, 4.2 log10 CCID50 of mumps virus, and 3.3 log10 CCID50 of rubella virus. Each dose also contains 32 mg of anhydrous lactose, 9 mg of sorbitol, 9 mg of amino acids, and 8 mg of mannitol. Each dose may also contain residual amounts of neomycin sulphate (≤25 mcg), ovalbumin (≤60 ng), and bovine serum albumin (≤50 ng), from the manufacturing process. After reconstitution, PRIORIX is a clear peach- to fuchsia pink-colored suspension.

PRIORIX contains no preservative.

The tip caps of the prefilled syringes of Sterile Water Diluent Component contain natural rubber latex. The plungers of the syringes and the stoppers of the Lyophilized Antigen Component, Live vials are not made with natural rubber latex.

12 CLINICAL PHARMACOLOGY

12.1 Mechanism of Action

Humoral immune responses against measles, mumps, and rubella viruses induced by PRIORIX were measured by enzyme-linked immunosorbent assays (ELISAs). IgG antibodies measured by the ELISAs used in clinical studies of PRIORIX have been shown to correlate with the presence of neutralizing antibodies that have been associated with protection [see Clinical Studies (14)].

13 NONCLINICAL TOXICOLOGY

13.1 Carcinogenesis, Mutagenesis, Impairment of Fertility

PRIORIX has not been evaluated for carcinogenic or mutagenic potential or for impairment of fertility.

14 CLINICAL STUDIES

The effectiveness of PRIORIX is based on a comparison of antibody responses relative to M‑M‑R II. Antibody responses to measles, mumps, and rubella viruses were measured by ELISAs. Analyses evaluated antibody geometric mean concentrations (GMC) and seroresponse rates (SRR). Seroresponse thresholds are 200 mIU/mL, 10 ELU/mL, and 10 IU/mL for anti-measles virus, anti-mumps virus, and anti-rubella virus antibodies, respectively.

14.1 Antibody Responses to Measles, Mumps and Rubella Viruses

Children 12 through 15 Months of Age Who Received PRIORIX as a First Dose

In Study 1 (NCT01702428), 5,003 participants 12 through 15 months of age received a first dose of PRIORIX (n = 3,714) or M‑M‑R II (n = 1,289) [see Adverse Reactions (6.1)]. Antibody responses to measles, mumps, and rubella viruses were measured by ELISAs using sera obtained 42 days following the first dose of either PRIORIX or M-M-R II. Non-inferiority of the immune response after the first dose of PRIORIX compared with M-M-R II was demonstrated in terms of SRR and GMC to measles, mumps, and rubella viruses. The immune responses measured in the U.S. study participants were similar to those in the overall study population. A summary of immune responses is shown in Table 4.

Table 4. Immune Responses after the First Dose of PRIORIX Compared with M-M-R II (Study 1, NCT01702428, According-to-Protocol Population)
Parameter | Virus Antigen | PRIORIX; N = 3,187-3,248 | M-M-R II; N = 1,107-1,137 | Difference; (PRIORIX minus; M-M-R II); (95% CI)
SRRa (%) | Measles | 98 | 98 | 0.18; (-0.68, 1.25)
SRRa (%) | Mumps | 98 | 98 | 0.81; (-0.10, 1.96)
SRRa (%) | Rubella | 97 | 99 | -1.15; (-2.00, -0.15)
 |  | PRIORIX; N = 3,187-3,248 | M-M-R II; N = 1,107-1,137 | Ratio; (PRIORIX / M-M-R II); (95% CI)
GMCb | Measles (mIU/mL) | 3,165 | 3,215 | 0.98; (0.93, 1.05)
GMCb | Mumps (ELU/mL) | 76 | 73 | 1.05; (0.99, 1.11)
GMCb | Rubella (IU/mL) | 53 | 60 | 0.87; (0.83, 0.92)
According-to-Protocol cohort included all vaccinated participants who met protocol-defined criteria for immunogenicity analysis.
PRIORIX or M-M-R II was administered concomitantly with HAVRIX and VARIVAX; U.S. participants also received PREVNAR 13.
N = Number of participants.
SRR = Seroresponse rate (percentage of initially seronegative participants with concentration above seroresponse threshold for each assay).
GMC = Geometric mean antibody concentration adjusted for country.
CI = Confidence Interval.
a Non-inferiority criterion met for all antigens (lower limit of 2-sided 95% CI for the difference [group receiving PRIORIX minus group receiving M-M-R II] was ≥-5%).
b Non-inferiority criterion met for all antigens (lower limit of 2-sided 95% CI for the ratio [group receiving PRIORIX over group receiving M-M-R II] was ≥0.67).

Children 12 through 15 Months of Age Who Received a Second Dose of PRIORIX 6 Weeks after the First Dose

In Study 2 (NCT01681992), 4,516 participants 12 through 15 months of age received a first dose of PRIORIX (n = 2,990) or M-M-R II (n = 1,526) followed by a second dose of the same vaccine 6 weeks later [see Adverse Reactions (6.1)]. Antibody responses to measles, mumps, and rubella viruses were measured in a subset of participants (n = 199 – 259 PRIORIX; n = 212 – 257 M‑M‑R II) in sera obtained 42 days following the second dose of either PRIORIX or M‑M‑R II. In a descriptive analysis, the immune response after a second dose was similar between the group receiving PRIORIX and the group receiving M-M-R II in terms of antibody SRR and GMC for all antigens.

Children 4 through 6 Years of Age Who Received PRIORIX as a Second Dose of Measles, Mumps, and Rubella Virus Vaccine

In Study 3 (NCT01621802), 4,007 participants 4 through 6 years of age received PRIORIX (n = 2,917) or M‑M‑R II (n = 1,090) as a second dose following administration of an initial dose of a combined measles, mumps, and rubella virus-containing vaccine in the second year of life [see Adverse Reactions (6.1)]. Prior to vaccination, the percentages of participants with antibody levels above the seroresponse thresholds were 98.0% for measles, 95.7% for mumps, and 98.7% for rubella. Antibody responses to measles, mumps, and rubella viruses were measured by ELISAs using sera obtained 42 days following of either PRIORIX or M‑M‑R II as a second dose. The non-inferiority of PRIORIX to M-M-R II when administered with KINRIX and VARIVAX was demonstrated in terms of SRR and GMC to measles, mumps, and rubella viruses at Day 42 (Table 5).

Table 5. Immune Responses to PRIORIX Compared with M-M-R II as a Second Dose in Children 4 through 6 Years of Age (Study 3, NCT01621802, According-to-Protocol Population)
Parameter | Virus Antigen | PRIORIX; N = 690-698 | M-M-R II; N = 245-250 | Difference; (PRIORIX minus; M-M-R II); (97.5% CI)
SRRa (%) | Measles | 100 | 100 | 0.00; (-0.72, 1.98)
SRRa (%) | Mumps | 100 | 100 | 0.00; (-0.72, 1.97)
SRRa (%) | Rubella | 100 | 100 | -0.14; (-0.98, 1.84)
 |  | PRIORIX; N = 690-691 | M-M-R-II; N = 245-248 | Ratio; (PRIORIX / M-M-R II); (97.5% CI)
GMCb | Measles (mIU/mL) | 4,285 | 4,333 | 0.99; (0.92, 1.06)
GMCb | Mumps (ELU/mL) | 171 | 188 | 0.91; (0.83, 1.00)
GMCb | Rubella (IU/mL) | 97 | 94 | 1.03; (0.97, 1.09)
According-to-Protocol cohort included all vaccinated participants who met protocol-defined criteria for immunogenicity analysis.
N = Number of participants.
SRR = Seroresponse rate (percentage of participants with concentration above seroresponse threshold for each assay).
GMC = Geometric mean antibody concentration adjusted for pre-vaccination concentration.
CI = Confidence Interval.
a Non-inferiority criterion met for all antigens (lower limit of 2-sided 97.5% CI for the difference [group receiving PRIORIX minus group receiving M-M-R II] was ≥-5%).
b Non-inferiority criterion met for all antigens (lower limit of 2-sided 97.5% CI for the ratio [group receiving PRIORIX over group receiving M-M-R II] was ≥0.67).

Individuals 7 Years of Age and Older Who Received PRIORIX as a Second Dose of Measles, Mumps, and Rubella Vaccine

In Study 4 (NCT02058563), 860 participants 7 years of age and older received PRIORIX (n = 426) or M‑M‑R II (n = 434) as a second dose following previous administration of a combined measles, mumps, and rubella virus-containing vaccine [see Adverse Reactions (6.1)]. Prior to vaccination, the percentages of participants with antibody levels above the seroresponse thresholds were 93.1% for measles, 88.0% for mumps, and 81.9% for rubella. Antibody responses to measles, mumps, and rubella viruses were measured in sera obtained 42 days following the second dose of either PRIORIX or M-M-R II. The non-inferiority of the immune response after the second dose of PRIORIX compared with M-M-R II was demonstrated in terms of SRR and antibody GMC to measles, mumps, and rubella antigens. A summary of immune responses is shown in Table 6.

Table 6. Immune Responses to PRIORIX as a Second Dose Compared with M-M-R II (Study 4, NCT02058563, According-to-Protocol Population)
Parameter | Virus Antigen | PRIORIX; N = 405 | M-M-R II; N = 414 | Difference; (PRIORIX minus; M-M-R II); (95% CI)
SRRa (%) | Measles | 99 | 99 | -0.51; (-2.22, 1.02)
SRRa (%) | Mumps | 98 | 100 | -1.25; (-3.10, 0.23)
SRRa (%) | Rubella | 100 | 100 | -0.25; (-1.57, 0.90)
 |  | PRIORIX; N = 404 | M-M-R II; N = 413 | Ratio; (PRIORIX / M‑M‑R II) (95% CI)
GMCb | Measles (mIU/mL) | 1,754 | 1,783 | 0.98; (0.89, 1.09)
GMCb | Mumps (ELU/mL) | 114 | 110 | 1.04; (0.94, 1.15)
GMCb | Rubella (IU/mL) | 76 | 74 | 1.03; (0.94, 1.12)
According-to-Protocol cohort included all vaccinated participants who met protocol-defined criteria for immunogenicity analysis.
N = Number of participants.
SRR = Seroresponse rate (percentage of participants with concentration above seroresponse threshold for each assay).
GMC = Geometric mean antibody concentration adjusted for gender, age, country, and pre‑vaccination concentration.
CI = Confidence Intervals.
a Non-inferiority criterion met for all antigens (lower limit of 2-sided 95% CI for the difference [group receiving PRIORIX minus group receiving M-M-R II] was ≥-5%).
b Non-inferiority criterion met for all antigens (lower limit of 2-sided 95% CI for the ratio [group receiving PRIORIX over group receiving M-M-R II] was ≥0.67).

14.2 Concomitant Administration

Concomitant Administration with HAVRIX, VARIVAX, and PREVNAR 13

The concomitant use of PRIORIX or M-M-R II with HAVRIX and VARIVAX was evaluated in Study 1 (NCT01702428) in children 12 through 15 months of age. All participants received PRIORIX or M-M-R II administered concomitantly with HAVRIX and VARIVAX. Children enrolled in the U.S. also received PREVNAR 13 concomitantly.

In subsets of participants in Study 1, immune responses to the antigens contained in HAVRIX, VARIVAX, and PREVNAR 13 were measured in sera obtained 42 days after concomitant administration of PRIORIX or M-M-R II. There was no evidence that PRIORIX interfered with the antibody responses to these vaccines relative to the antibody responses when M-M-R II was concomitantly administered.

Concomitant Administration with KINRIX and VARIVAX

The concomitant use of PRIORIX or M-M-R II with KINRIX and VARIVAX was evaluated in Study 3 (NCT01621802) in children 4 through 6 years of age. A subset of participants received PRIORIX or M-M-R II administered concomitantly with KINRIX and VARIVAX.

Immune responses to the antigens contained in KINRIX and VARIVAX were measured in sera obtained 42 days after concomitant administration of PRIORIX or M‑M‑R II. There was no evidence that PRIORIX interfered with the antibody responses to these vaccines relative to the antibody responses when M-M-R II was concomitantly administered.

15 REFERENCES

1. Centers for Disease Control and Prevention. Measles, Mumps, and Rubella- Vaccine Use and Strategies for Elimination of Measles, Rubella, and Congenital Rubella Syndrome and Control of Mumps: Recommendations of the Advisory Committee on Immunization Practices (ACIP). MMWR. 2013; 62(4);1-34.
2. Eberhart-Phillips, J.E.; et al: Measles in pregnancy: a descriptive study of 58 cases. Obstetrics and Gynecology, 82(5): 797-801, November 1993.
3. Jespersen, C.S.; et al: Measles as a cause of fetal defects: A retrospective study of ten measles epidemics in Greenland. Acta Paediatr Scand. 66: 367-372, May 1977.
4. Bouthry, E.; Queinnec, C.; Vauzelle, C.; Vauloup‑Fellous, C.: Congenital rubella syndrome following rubella vaccination during pregnancy. Pediatrics. 2023; 152 (3): e2022057627.
5. Losonsky, G.A.; Fishaut, J.M.; Strussenber, J.; Ogra, P.L.: Effect of immunization against rubella on lactation products. II. Maternal-neonatal interactions, J. Infect. Dis. 145: 661-666, 1982.
6. Losonsky, G.A.; Fishaut, J.M.; Strussenber, J.; Ogra, P.L.: Effect of immunization against rubella on lactation products. I. Development and characterization of specific immunologic reactivity in breast milk, J. Infect. Dis. 145: 654-660, 1982.
7. Landes, R.D.; Bass, J.W.; Millunchick, E.W.; Oetgen, W.J.: Neonatal rubella following postpartum maternal immunization, J. Pediatr. 97: 465-467, 1980.
8. Lerman, S.J.: Neonatal rubella following postpartum maternal immunization, J. Pediatr. 98: 668, 1981. (Letter)

16 HOW SUPPLIED/STORAGE AND HANDLING

PRIORIX is supplied in a box (NDC 58160-824-15) containing:

- 10 single-dose vials of Lyophilized Antigen Component, Live: NDC 58160-831-03
- 10 single-dose prefilled ungraduated syringes of Sterile Water Diluent Component (packaged without needles): NDC 58160-833-02

After reconstitution, each vial contains one dose (approximately 0.5 mL) of PRIORIX.

16.1 Storage before Reconstitution

Vials of Lyophilized Antigen Component, Live: Store refrigerated between 36° and 46°F (2° and 8°C). Protect vials from light.

Prefilled ungraduated syringes of Sterile Water Diluent Component: Store refrigerated between 36° and 46°F (2° and 8°C) or at controlled room temperature up to 77°F (25°C).

Do not freeze Lyophilized Antigen Component, Live or Sterile Water Diluent Component.

16.2 Storage after Reconstitution

Administer PRIORIX immediately after reconstitution. If not used immediately, store refrigerated between 36° and 46°F (2° and 8°C) and administer within 8 hours. Discard reconstituted vaccine if not used within 8 hours.

Do not freeze. Discard if the reconstituted vaccine has been frozen.

17 PATIENT COUNSELING INFORMATION

- Inform vaccine recipients, parents, or guardians of the potential benefits and risks of vaccination with PRIORIX.
- Question individuals of reproductive potential regarding the possibility of pregnancy prior to administration of PRIORIX. Instruct these individuals to avoid pregnancy for 1 month following vaccination [see Contraindications (4.3), Use in Specific Populations (8.1)].
- Inform vaccine recipients, parents, or guardians about the potential for adverse reactions that have been observed following administration of PRIORIX.
- Provide the Vaccine Information Statements, which are available free of charge at the U.S. Centers for Disease Control and Prevention (CDC) website (www.cdc.gov/vaccines).

PRIORIX, HAVRIX, and KINRIX are trademarks owned by or licensed to the GSK group of companies.

The other brands listed are trademarks owned by or licensed to their respective owners and are not owned by or licensed to the GSK group of companies. The makers of these brands are not affiliated with and do not endorse the GSK group of companies or its products.

Manufactured by GlaxoSmithKline Biologicals

Rixensart, Belgium, U.S. License 1617

Distributed by GlaxoSmithKline, Durham, NC 27701

©2025 GSK group of companies or its licensor.

PRX:3PI

PACKAGE LABEL

NDC 58160-824-15

PRIORIX

Measles, Mumps, and Rubella Vaccine, Live

MMR

Rx only

NOTICE: Reconstitue Lyophilized Antigen Component, Live with Sterile Water Diluent Component before use

For 12 Months of Age and Older

Contents: 10 Doses of PRIORIX

- 10 single-dose vials of Lyophilized Antigen Component, Live
- 10 single-dose prefilled ungraduated syringes of Sterile Water Diluent Component

After reconstitution, a single dose of PRIORIX is approximately 0.5 mL

For subcutaneous injection only.
GSK
PRIORIX
©2024 the GSK group of companies or its licensor.
Rev. 04/24
519679